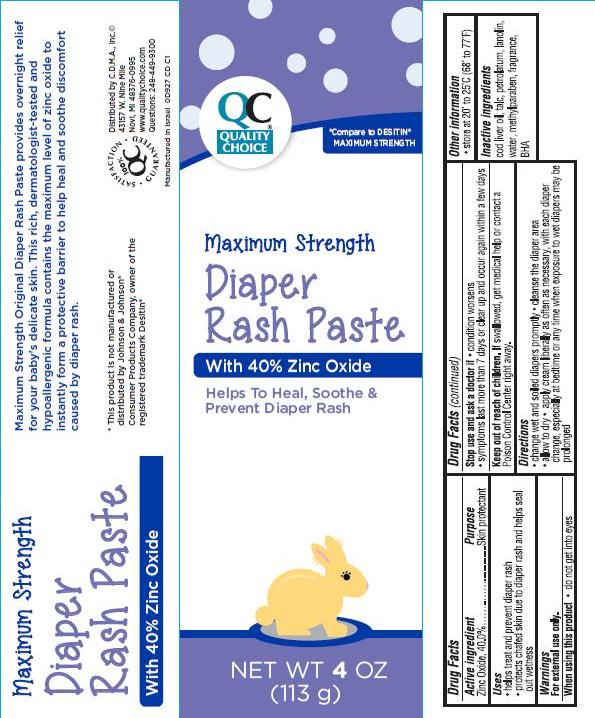 DRUG LABEL: Quality Choice Maximum Strength Diaper Rash
NDC: 63868-165 | Form: CREAM
Manufacturer: Chain Drug Marketing Association
Category: otc | Type: HUMAN OTC DRUG LABEL
Date: 20140408

ACTIVE INGREDIENTS: ZINC OXIDE 40 g/100 g
INACTIVE INGREDIENTS: COD LIVER OIL; TALC; PETROLATUM; LANOLIN; WATER; METHYLPARABEN; BUTYLATED HYDROXYANISOLE

Maximum Strength Diaper Rash Paste

Active ingredient

Zinc Oxide, 40.0%

Purpose

Skin protectant

Uses

- helps treat and prevent diaper rash
- protects chafed skin due to diaper rash and helps seal out wetness

Warnings

For external use only.

When using this product

- do not get into eyes

Stop use and ask a doctor if

- condition worsens
- symptoms last more than 7 days or clear up and occur again within a few days

Keep Out of Reach of Children.

If swallowed, get medical help or contact a Poison Control Center right away.

Directions

- change wet and soiled diapers promptly
- cleanse the diaper area
- allow to dry
- apply cream liberally as often as necessary, with each diaper change, especially at bedtime or any time when exposure to wet diapers may be prolonged

Other Information

- store at 20° to 25°C (68° to 77°F)

Inactive ingredients

cod liver oil, talc, petrolatum, lanolin, water, methylparaben, fragrance, BHA

Package/Label Principal Display Panel

Maximum Strength Diaper Rash Paste
With 40% Zinc Oxide

Helps To Heal, Soothe & Prevent Diaper Rash

NET WT 4 OZ. (113 g)

*Compare to DESITIN® MAXIMUM STRENGTH

Maximum Strength Original Diaper Rash Paste provides overnight relief for your baby's delicate skin. This rich, dermatologist-tested and hypoallergenic formula contains the maximum level of zinc oxide to instantly form a protective barrier to help heal and soothe discomfort caused by diaper rash.

*This product is not manufactured or distributed by Johnson & Johnson®
Consumer Products Company, owner of the registered trademark Desitin®

Distributed by C.D.M.A., Inc.©
43157 W. Nine Mile
Novi, MI 48376-0995
www.qualitychoice.com
Questions: 248-449-9300

Manufactured in Israel
0D927 CD C1

SATISFACTION GUARANTEED

Carton Label